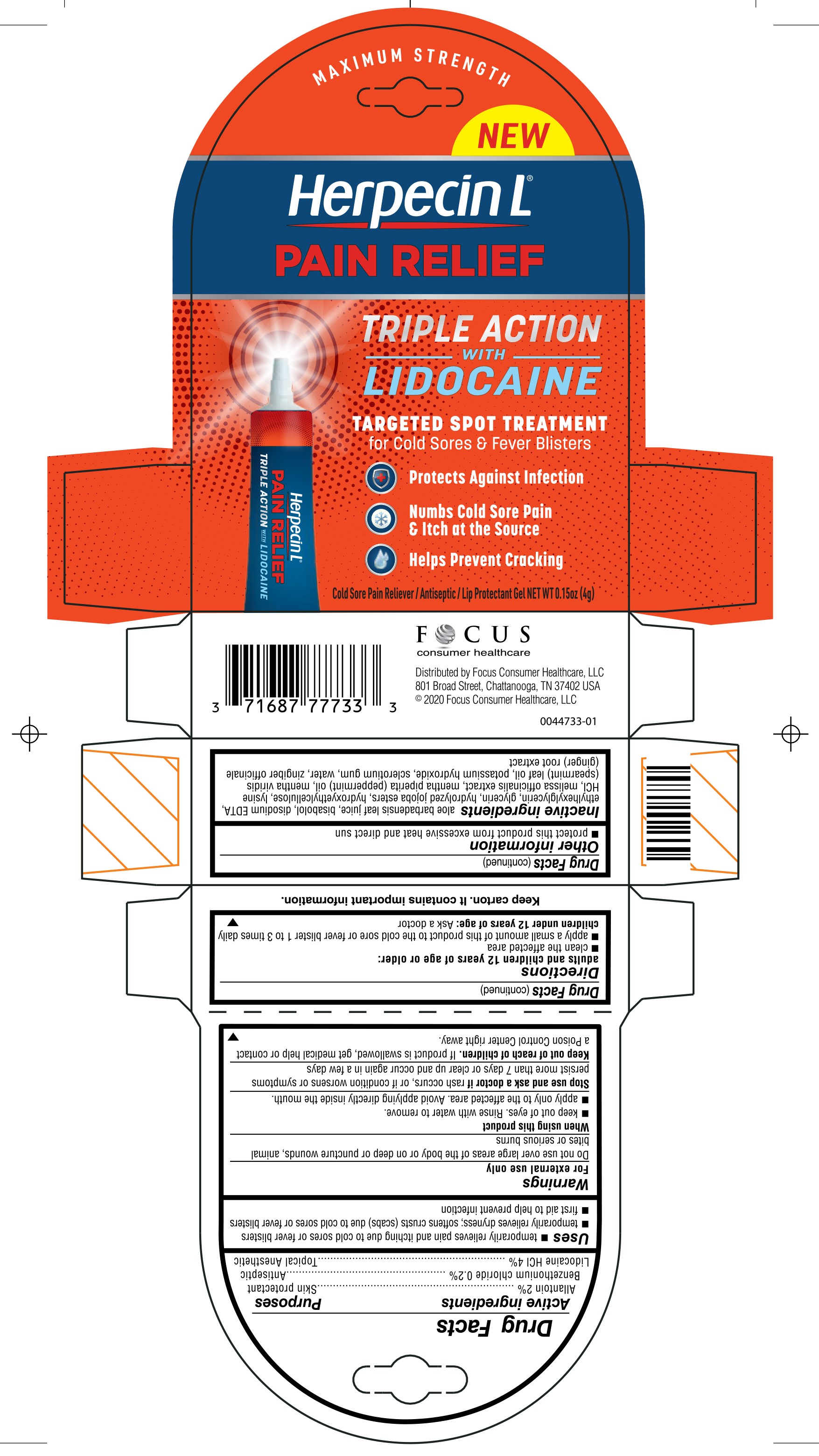 DRUG LABEL: Herpecin Pain Relief
NDC: 71687-4000 | Form: GEL
Manufacturer: Focus Consumer Healthcare, LLC
Category: otc | Type: HUMAN OTC DRUG LABEL
Date: 20250414

ACTIVE INGREDIENTS: LIDOCAINE HYDROCHLORIDE ANHYDROUS 4 g/100 g; ALLANTOIN 2 g/100 g; BENZETHONIUM CHLORIDE 0.2 g/100 g
INACTIVE INGREDIENTS: HYDROXYETHYL CELLULOSE, UNSPECIFIED; LYSINE HYDROCHLORIDE, DL-; ETHYLHEXYLGLYCERIN; ALOE VERA LEAF; LEVOMENOL; EDETATE DISODIUM; GLYCERIN; WATER; GINGER; HYDROLYZED JOJOBA ESTERS (ACID FORM); SPEARMINT OIL; MELISSA OFFICINALIS; MENTHA PIPERITA; POTASSIUM HYDROXIDE; BETASIZOFIRAN

Herpecin Pain Relief

ACTIVE INGREDIENT

Allantoin 2%
Benzethonium chlroide 0.2%
Lidocaine HCl 4%

PURPOSE

Skin Protectant

Antiseptic

Topical Anesthetic

USES

■ temporarily relieves pain and itching due to cold sores or fever blisters

■ temporarily relieves dryness; softens crusts (scabs) due to cold sores or fever blisters

■ first aid to help prevent infection in minor cuts, scrapes or burns due to cold sores or fever blisters

WARNINGS

For external use only

Do not use over large areas of the body or on deep or puncture wounds, animal bites or serious burns

WHEN USING THIS PRODUCT

■ keep out of eyes. Rinse with water to remove.

■ apply only to the affected area. Avoid applying directly inside the mouth.

Stop use and ask a doctor if rash occurs, or if condition worsens or symptoms persist more than 7 days or clear up and occur again in a few days

Keep out of reach of children. If product is swallowed, get medical help or contact a Poison Control Center right away.

DIRECTIONS

adults and children 12 years of age or older:

■ clean the affected area

■ apply externally to the lips 1 to 3 times daily

children under 12 years of age: Ask a doctor

OTHER INFORMATION

■ protect this product from excessive heat and direct sun

■ keep this carton as it contains important information

INACTIVE INGREDIENT

aloe barbadensis leaf juice, bisabolol, disodium EDTA, ethylhexylglycerin, glycerin, hydrolyzed jojoba esters, hydroxyethylcellulose, lysine HCl, melissa officinalis extract, mentha piperita (peppermint) oil, mentha viridis (spearmint) leaf oil, potassium hydroxide, sclerotium gum, water, zingiber officinale (ginger) root extract

Principal Display Panel

Maximum Strength - NEW

Herpecin L

Pain Relief

Triple Action with Lidocain

Tageted Spot Treatment

for Cold Sores & Fever Blisters

Protects Against Infection

Numbs Cold Sore Pain & Itch at the Source

Helps Preven Cracking

Cold Sore Pain Reliever/Antiseptic/Lop Protectant Gel NET WT 0.15oz (4g)